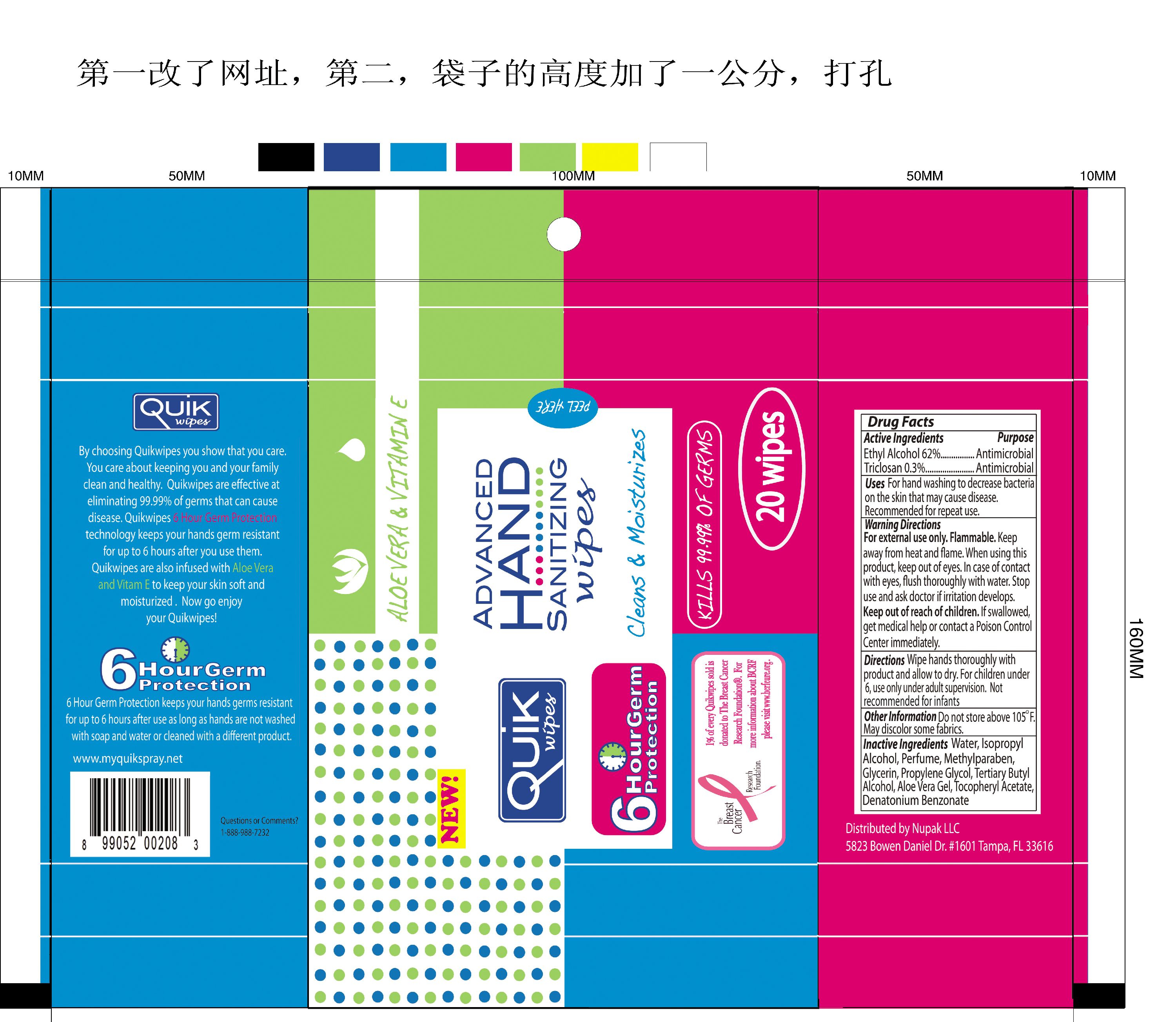 DRUG LABEL: Quik Wipes
NDC: 41900-400 | Form: SWAB
Manufacturer: Cinogen Cosmetics Zhaoqing, LTD.
Category: otc | Type: HUMAN OTC DRUG LABEL
Date: 20090908

ACTIVE INGREDIENTS: ALCOHOL 0.62 1/1 1; TRICLOSAN 0.003 1/1 1
INACTIVE INGREDIENTS: WATER; ISOPROPYL ALCOHOL; METHYLPARABEN; GLYCERIN; PROPYLENE GLYCOL; TERT-BUTYL ALCOHOL; ALOE VERA LEAF; ALPHA-TOCOPHEROL ACETATE; DENATONIUM BENZOATE

QuikWipes Advanced Hand Sanitizing Wipes

Active Ingredients Purpose

Ethyl Alcohol 62 percent Antimicrobial

Triclosan 0.3 percent Antimicrobial

PURPOSE

Uses For hand washing to decrease bacteria on the skin that may cause disease.

Recommended for repeat use.

WARNINGS AND PRECAUTIONS

Warning Directions

For external use only. Flammable.

Keep away from heat and flame. When using this product, keep out of eyes. In case of contact with eyes, flush thoroughly with water.

Stop use and ask doctor if irritation develops.

Keep out of reach of children.

If swallowed get medical help or contact a Poison Control Center immediately.

INDICATIONS AND USAGE

Directions Wipe hands thoroughly with product and allow to dry.

For children under 6, use only under adult supervision.

Not recommended for infants

USER SAFETY WARNINGS

Do not store above 105 degrees F.

May discolor some fabrics.

Inactive Ingredients

Water, Isopropyl Alcohol, Perfume, Methylparaben, Glycerin, Propylene Glycol,

Tertiary Butyl Alcohol, Aloe Vera Gel, Tocopheryl Acetate, Denatonium Benzonate